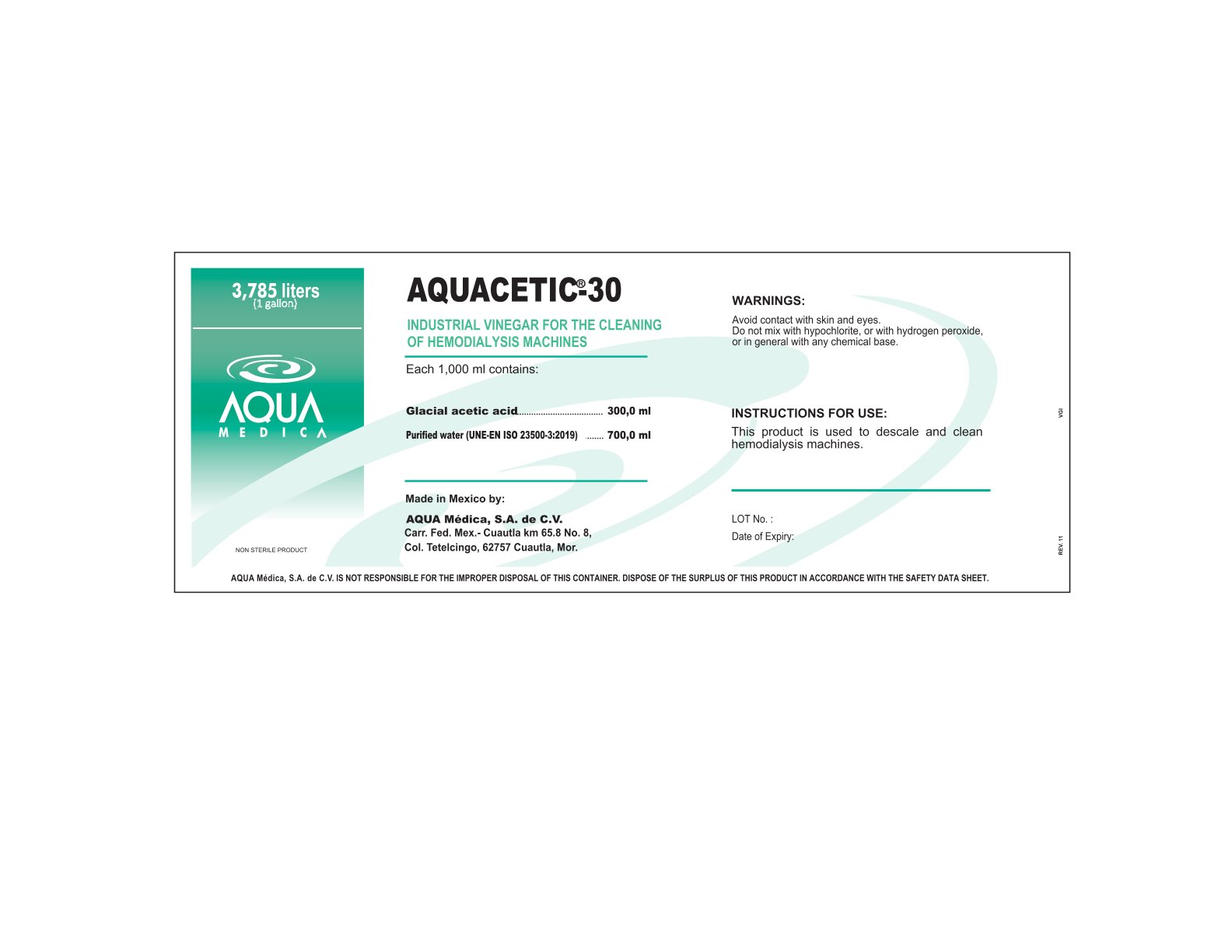 DRUG LABEL: AQUACETIC-30
NDC: 81943-801 | Form: SOLUTION, CONCENTRATE
Manufacturer: Aqua Medica, S.A. de C.V.
Category: otc | Type: HUMAN OTC DRUG LABEL
Date: 20251110

ACTIVE INGREDIENTS: CITRIC ACID MONOHYDRATE 0.3 g/100 mL
INACTIVE INGREDIENTS: WATER 0.7 g/100 mL

INDUSTRIAL VINEGAR FOR THE CLEANING
OF HEMODIALYSIS MACHINES

ACTIVE INGREDIENT

Glacial Acetic Acid

PURPOSE

This product is used to descale and clean
hemodialysis machines.

INDICATIONS AND USAGE

For use with 3-pump hemodialysis machines only, using purified water.

WARNINGS

Avoid contact with skin and eyes.
Do not mix with hypochlorite, or with hydrogen peroxide,
or in general with any chemical base.

DO NOT USE

Do not mix with hypochlorite, or with hydrogen peroxide,
or in general with any chemical base.

WHEN USING

Take appropriate security measures (protective clothing, glasses, masks).

STOP USE

If you do not use the entire contents, discard the excess.

Keep out of reach of children. If swallowed, get medical help or contact a Poison Control Center right away.

DOSAGE AND ADMINISTRATION

This product is used to descale and clean
hemodialysis machines.

STORAGE AND HANDLING

Store at room temperature.

Keep container tightly closed when not in use.

INACTIVE INGREDIENT

Water.

PACKAGE LABEL

81943-801-01